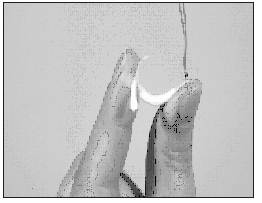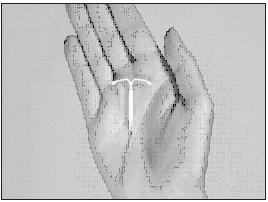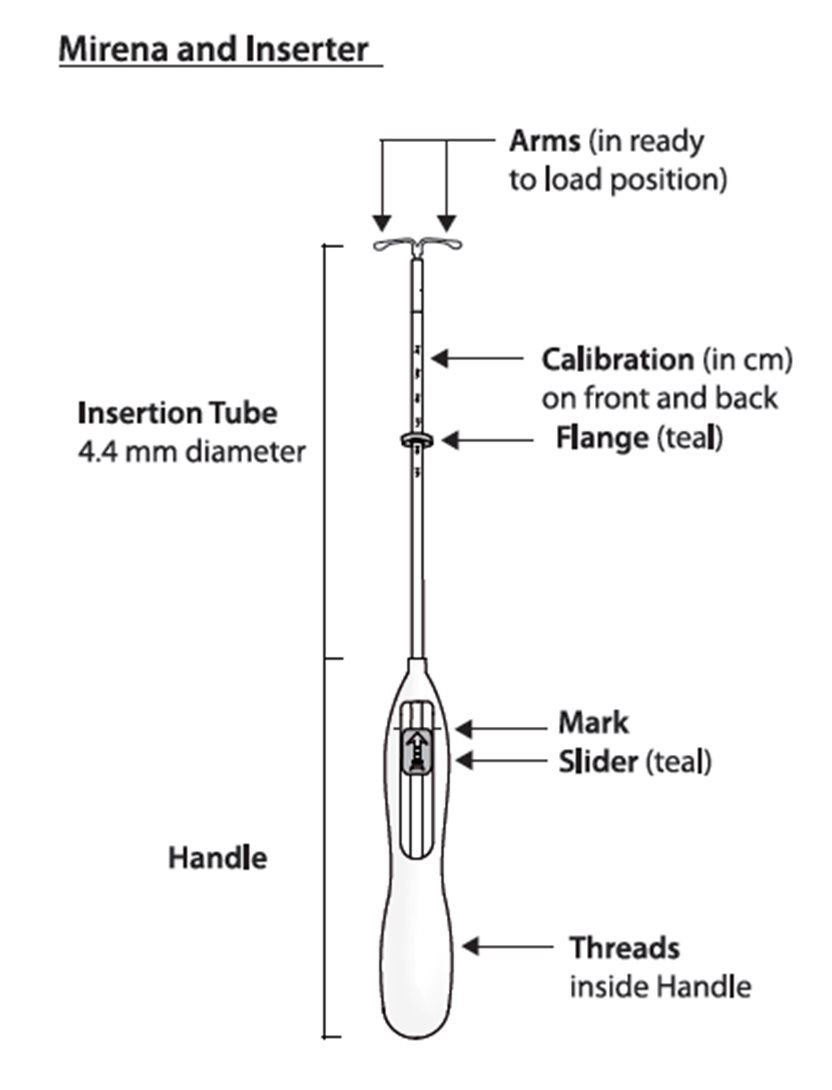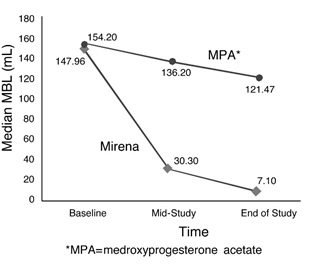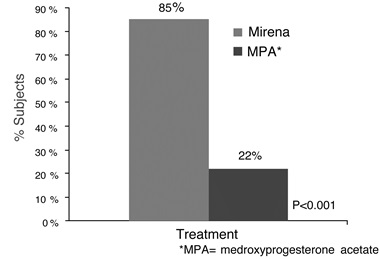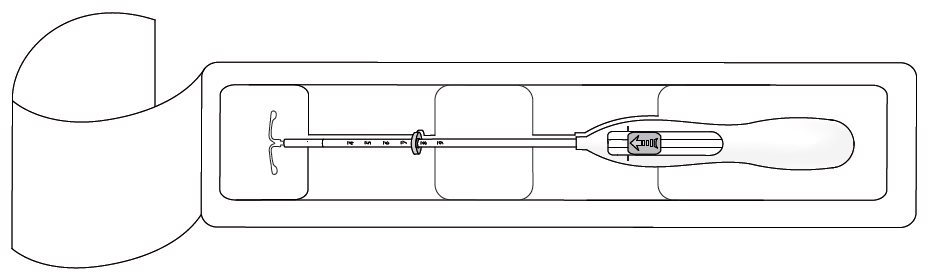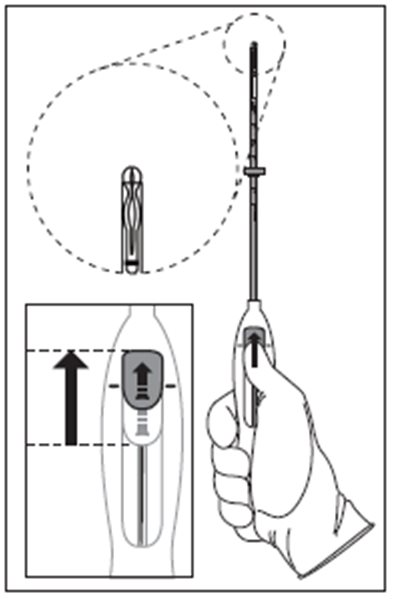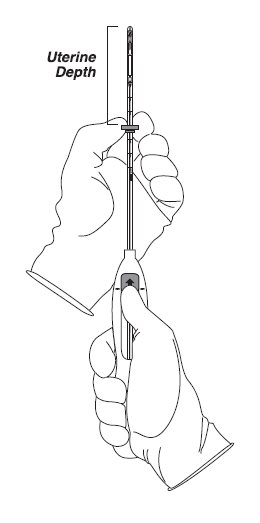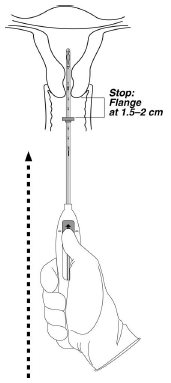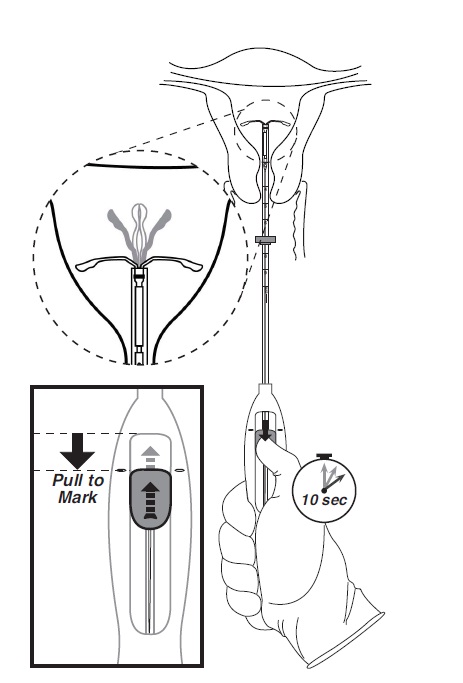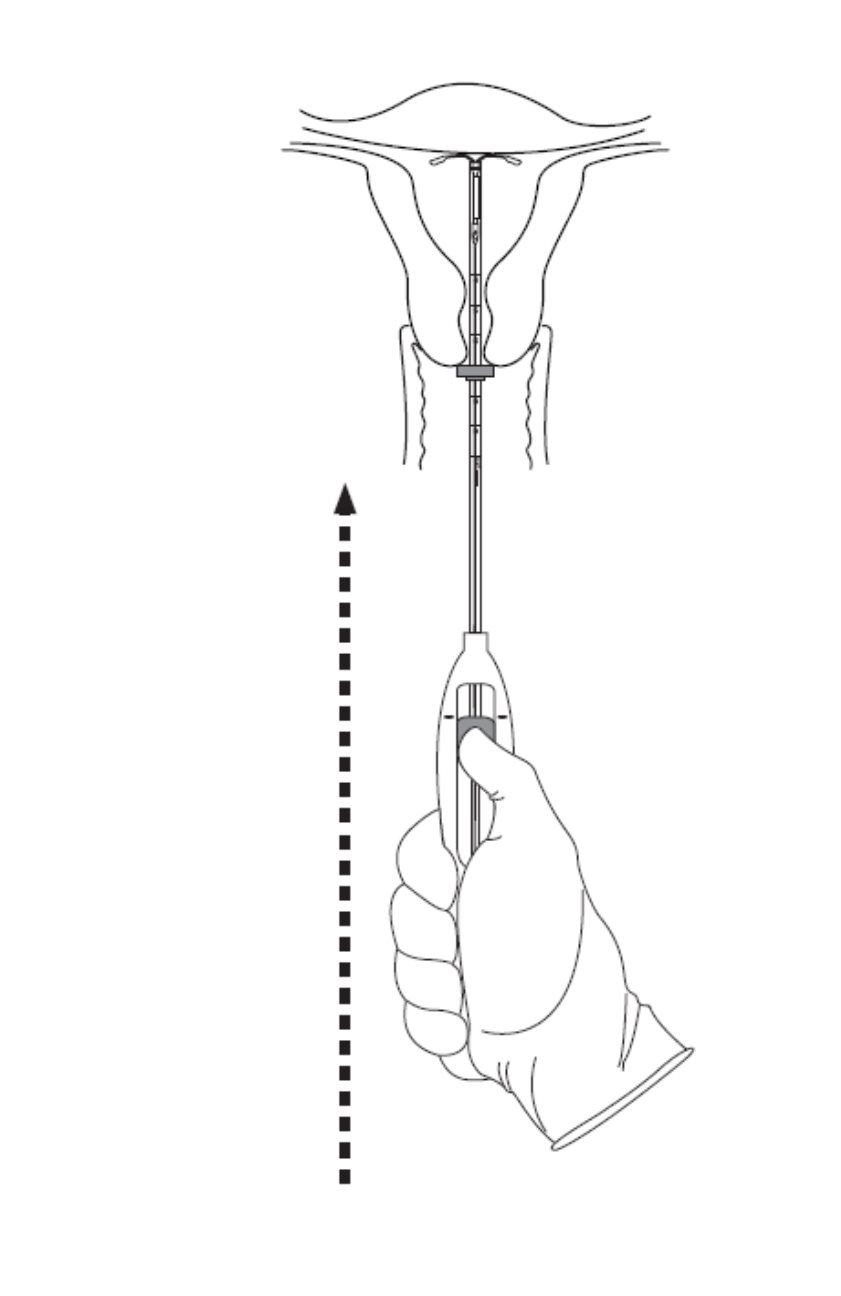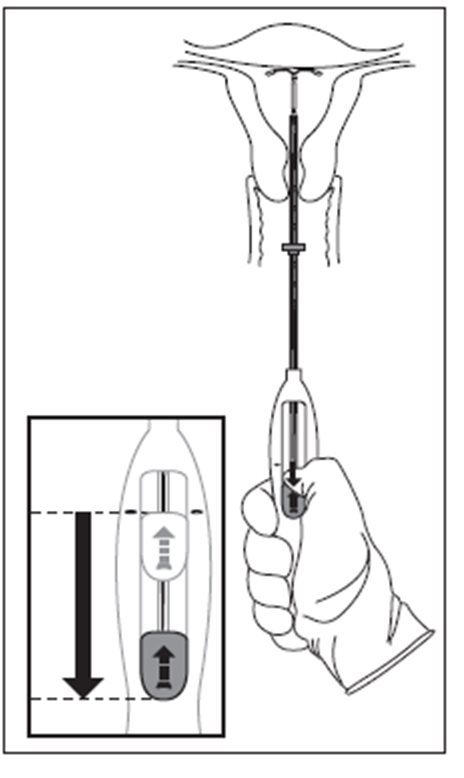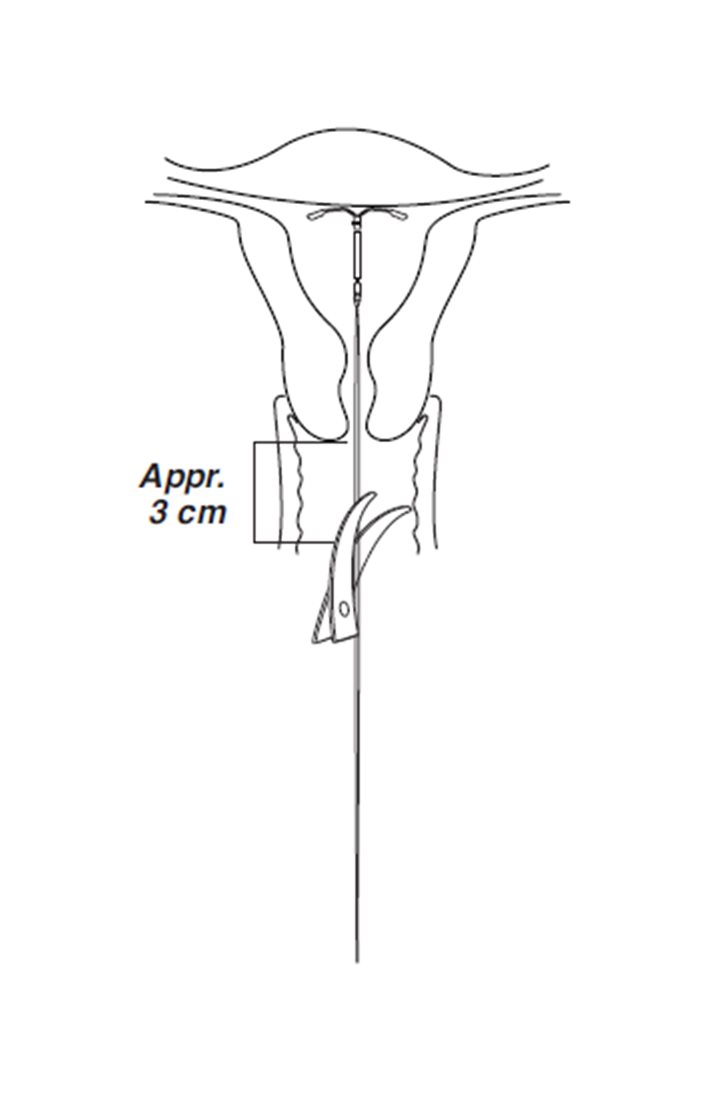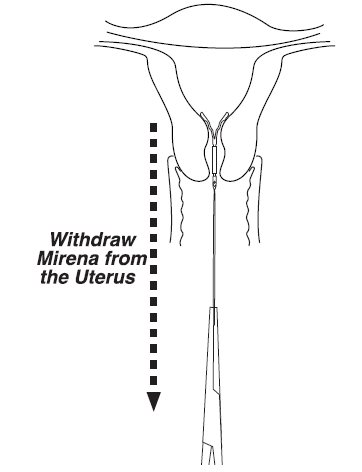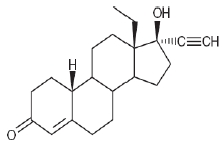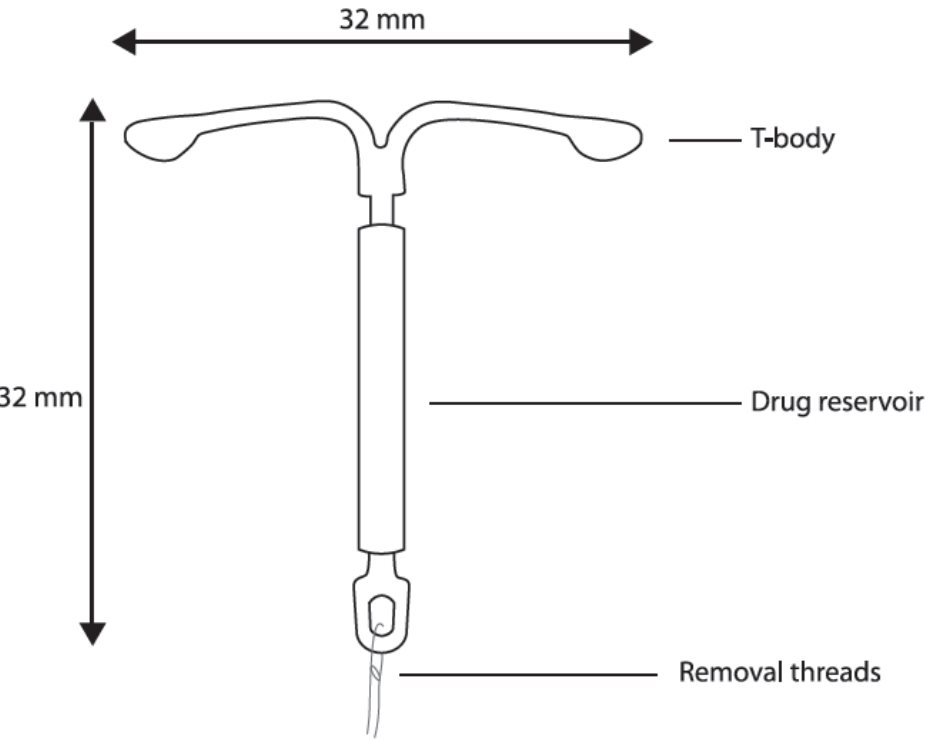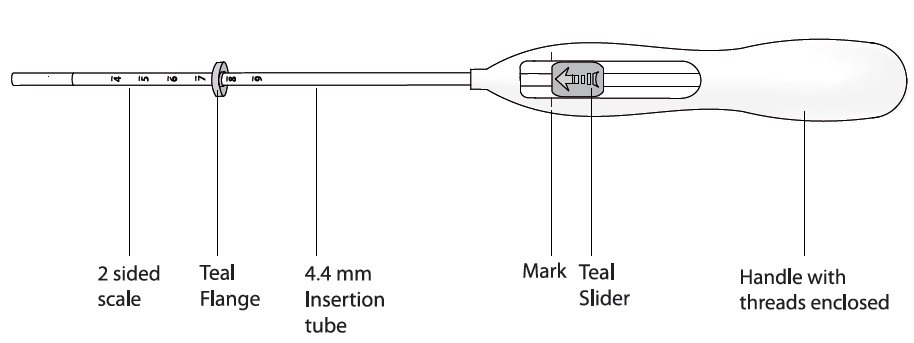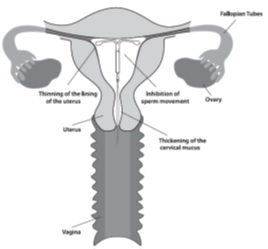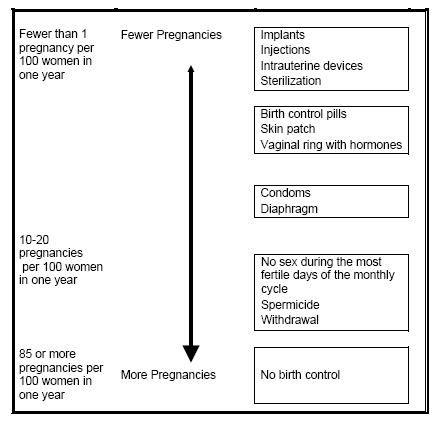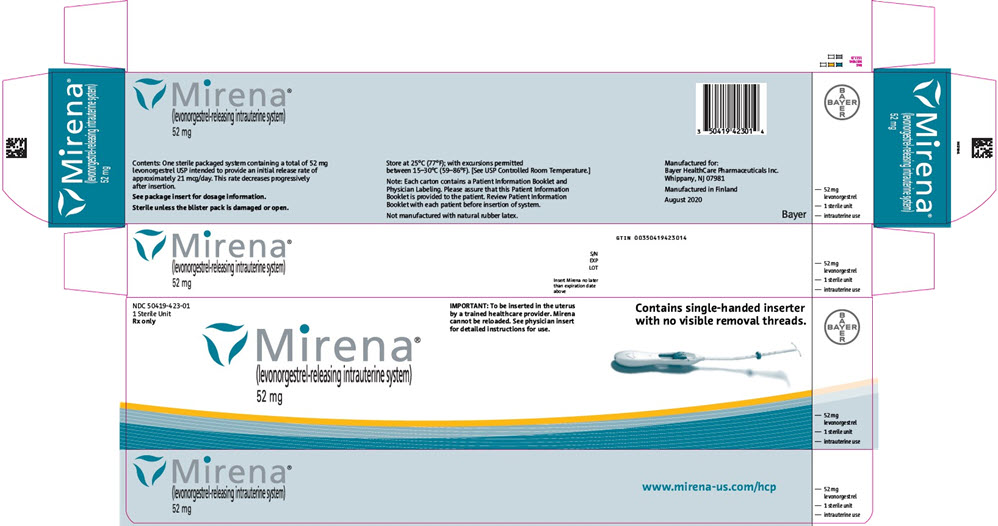 DRUG LABEL: Mirena
NDC: 50419-423 | Form: INTRAUTERINE DEVICE
Manufacturer: Bayer HealthCare Pharmaceuticals Inc.
Category: prescription | Type: HUMAN PRESCRIPTION DRUG LABEL
Date: 20251029

ACTIVE INGREDIENTS: LEVONORGESTREL 52 mg/1 1
INACTIVE INGREDIENTS: DIMETHICONE, UNSPECIFIED; BARIUM SULFATE

HIGHLIGHTS OF PRESCRIBING INFORMATION

These highlights do not include all the information needed to use MIRENA safely and effectively. See full prescribing information for MIRENA.
MIRENA (levonorgestrel-releasing intrauterine system)
Initial U.S. Approval: 2000

1 INDICATIONS AND USAGE

Mirena is a progestin-containing intrauterine system (IUS) indicated for:

- Prevention of pregnancy for up to 8 years (1.1)
- Treatment of heavy menstrual bleeding for women who choose to use intrauterine contraception as their method of contraception for up to 5 years. (1.2)

2 DOSAGE AND ADMINISTRATION

- Release rate of levonorgestrel (LNG) is 21 mcg/day after 24 days; this rate is reduced to about 11 mcg/day after 5 years and 7 mcg/day after 8 years. (2.1)
- To be inserted by a trained healthcare provider using strict aseptic technique. Follow insertion instructions exactly as described. (2.2)
- Patient should be re-examined and evaluated 4 to 6 weeks after insertion; then, yearly or more often if clinically indicated. (2.3)

3 DOSAGE FORMS AND STRENGTHS

- One sterile intrauterine system consisting of a T-shaped polyethylene frame with a steroid reservoir containing 52 mg levonorgestrel packaged within a sterile inserter (3)

4 CONTRAINDICATIONS

- Pregnancy or suspicion of pregnancy. Cannot be used for post-coital contraception (emergency contraception) (4).
- Congenital or acquired uterine anomaly if it distorts the uterine cavity (4)
- Acute pelvic inflammatory disease (PID) or a history of PID unless there has been a subsequent intrauterine pregnancy (4)
- Postpartum endometritis or infected abortion in the past 3 months (4)
- Known or suspected uterine or cervical malignancy (4)
- Known or suspected breast cancer or other progestin-sensitive cancer (4)
- Uterine bleeding of unknown etiology (4)
- Untreated acute cervicitis or vaginitis or other lower genital tract infections (4)
- Acute liver disease or liver tumor (benign or malignant) (4)
- Increased susceptibility to pelvic infection (4)
- A previous intrauterine device (IUD) that has not been removed (4)
- Hypersensitivity to any component of Mirena (4)

5 WARNINGS AND PRECAUTIONS

- Remove Mirena if pregnancy occurs with Mirena in place. If pregnancy occurs, there is increased risk of ectopic pregnancy including loss of fertility, pregnancy loss, septic abortion (including septicemia, shock and death), and premature labor and delivery. (5.1, 5.2)
- Group A streptococcal infection has been reported following insertion of LNG IUS; strict aseptic technique is essential during insertion. (5.3)
- Before using Mirena, consider the risks of PID. (5.4)
- Uterine perforation may occur and may reduce contraceptive effectiveness or require surgery. Risk is increased if inserted in lactating women and may be increased if inserted in women with fixed retroverted uteri or postpartum. (5.5)
- Partial or complete expulsion may occur, which can be unnoticed, leading to loss of contraceptive efficacy. (5.6)
- Evaluate persistent enlarged ovarian follicles or ovarian cysts. (5.7)
- Bleeding patterns become altered, may remain irregular and amenorrhea may ensue. (5.8)

6 ADVERSE REACTIONS

The most common adverse reactions (≥10% users) are alterations of menstrual bleeding patterns, abdominal/pelvic pain, amenorrhea, headache/migraine, genital discharge, and vulvovaginitis. (6.1)

To report SUSPECTED ADVERSE REACTIONS, contact Bayer HealthCare Pharmaceuticals Inc. at 1-888-842-2937 or FDA at 1-800-FDA-1088 or www.fda.gov/medwatch.

FULL PRESCRIBING INFORMATION

1 INDICATIONS AND USAGE

1.1 Contraception

Mirena is indicated for prevention of pregnancy for up to 8 years; replace after the end of the eighth year.

1.2 Heavy Menstrual Bleeding

Mirena is indicated for the treatment of heavy menstrual bleeding for up to 5 years in women who choose to use intrauterine contraception as their method of contraception; replace after the end of the fifth year if continued treatment of heavy menstrual bleeding is needed.

2 DOSAGE AND ADMINISTRATION

2.1 Dosing Over Time

Mirena contains 52 mg of levonorgestrel (LNG) released in vivo, at a rate of approximately 21 mcg/day after 24 days. This rate decreases progressively to approximately 11 mcg/day after 5 years and 7 mcg/day after 8 years.

For contraception, remove Mirena by the end of the eighth year and replace at the time of removal with a new Mirena if continued use is desired.

For treatment of heavy menstrual bleeding, replace Mirena by the end of the fifth year if continued use is needed because data on use in this indication beyond 5 years are limited.

Mirena is supplied in a sterile package within an inserter that enables single-handed loading (see Figure 1). Do not open the package until required for insertion [see Description (11.2)]. Do not use if the seal of the sterile package is broken or appears compromised. Use strict aseptic techniques throughout the insertion procedure [see Warnings and Precautions (5.3)].

2.2 Insertion Instructions

- Obtain a complete medical and social history to determine conditions that might influence the selection of a levonorgestrel-releasing intrauterine system (LNG IUS) for contraception. If indicated, perform a physical examination, and appropriate tests for any forms of genital or other sexually transmitted infections. [See Contraindications (4) and Warnings and Precautions (5.10).] Because irregular bleeding/spotting is common during the first months of Mirena use, exclude endometrial pathology (polyps or cancer) prior to the insertion of Mirena in women with persistent or uncharacteristic bleeding [see Warnings and Precautions (5.8)].
- Follow the insertion instructions exactly as described to ensure proper placement and avoid premature release of Mirena from the inserter. Once released, Mirena cannot be re-loaded.
- Check expiration date of Mirena prior to initiating insertion.

- Mirena should be inserted by a trained healthcare provider. Healthcare providers should become thoroughly familiar with the insertion instructions before attempting insertion of Mirena.
- Insertion may be associated with some pain and/or bleeding or vasovagal reactions (for example, syncope, bradycardia), or with seizure, especially in patients with a predisposition to these conditions. Consider administering analgesics prior to insertion.

Timing of Insertion

Table 1: When to Insert Mirena
Starting Mirena in women not currently using hormonal or intrauterine contraception | - Insert Mirena any time there is reasonable certainty that the woman is not pregnant. Consider the possibility of ovulation and conception prior to initiation of this product [see Contraindications (4)]. - If Mirena is inserted during the first seven days of the menstrual cycle or immediately after a first trimester abortion, back-up contraception is not needed. - If Mirena is not inserted during the first seven days of the menstrual cycle, a barrier method of contraception should be used, or the patient should abstain from vaginal intercourse for seven days to prevent pregnancy.
Switching to Mirena from an oral, transdermal, or vaginal hormonal contraceptive | - Insert Mirena at any time, including during the hormone-free interval of the previous method. - If inserted during active use of the previous method, continue that method for 7 days after Mirena insertion or until the end of the current treatment cycle. - If the woman was using continuous hormonal contraception, discontinue that method seven days after Mirena insertion.
Switching to Mirena from an injectable progestin contraceptive | - Insert Mirena at any time; a non-hormonal back-up birth control (such as condoms or spermicide) should also be used for 7 days if Mirena is inserted more than 3 months (13 weeks) after the last injection.
Switching to Mirena from a contraceptive implant or another IUS | - Insert Mirena on the same day the implant or IUS is removed. - Insert Mirena at any time during the menstrual cycle.
Inserting Mirena after first-trimester abortion or miscarriage | - Insert Mirena immediately after a first-trimester abortion or miscarriage, unless it is a septic abortion [see Contraindications (4)].
Inserting Mirena after childbirth or second-trimester abortion or miscarriage
- Immediate insertion after childbirth or second-trimester abortion or miscarriage | - Insert Mirena after removal of the placenta. Back-up contraception is not needed. [See Contraindications (4), Warnings and Precautions (5.5, 5.6), Adverse Reactions (6.2)].
Interval insertion following complete involution of the uterus | - Wait a minimum of 6 weeks or until the uterus is fully involuted before inserting Mirena [see Warnings and Precautions (5.5, 5.6), Adverse Reactions (6.2)]. - Insert Mirena any time there is reasonable certainty the woman is not pregnant. - If Mirena is not inserted during the first 7 days of the menstrual cycle, a back-up method of contraception should be used, or the woman should abstain from vaginal intercourse for 7 days to prevent pregnancy [see Contraindications (4), Warnings and Precautions (5.2)].

Tools for Insertion

Note: The inserter provided with Mirena (see Figure 1) and the Insertion Procedure described in this section are not applicable for immediate insertion after childbirth or second-trimester abortion or miscarriage. For immediate insertion, remove Mirena from the inserter by first loading (see Figure 2) and then releasing (see Figure 7) Mirena from the inserter, and insert according to accepted practice.

Preparation

- Gloves
- Speculum
- Sterile uterine sound
- Sterile tenaculum
- Antiseptic solution, applicator

Procedure

- Sterile gloves
- Mirena with inserter in sealed package
- Instruments and anesthesia for paracervical block, if anticipated
- Consider having an unopened back-up Mirena available
- Sterile, sharp curved scissors

Preparation for insertion

- Exclude pregnancy and confirm that there are no other contraindications to the use of Mirena.
- With the patient comfortably in lithotomy position, do a bimanual exam to establish the size, shape and position of the uterus.
- Gently insert a speculum to visualize the cervix.
- Thoroughly cleanse the cervix and vagina with a suitable antiseptic solution.
- Prepare to sound the uterine cavity. Grasp the upper lip of the cervix with a tenaculum forceps and gently apply traction to stabilize and align the cervical canal with the uterine cavity. Perform a paracervical block if needed. If the uterus is retroverted, it may be more appropriate to grasp the lower lip of the cervix. The tenaculum should remain in position and gentle traction on the cervix should be maintained throughout the insertion procedure.
- Gently insert a uterine sound to check the patency of the cervix, measure the depth of the uterine cavity in centimeters, confirm cavity direction, and detect the presence of any uterine anomaly. If you encounter difficulty or cervical stenosis, use dilatation, and not force, to overcome resistance. If cervical dilatation is required, consider using a paracervical block.
- The uterus should sound to a depth of 6 to 10 cm. Insertion of Mirena into a uterine cavity less than 6 cm by sounding may increase the incidence of expulsion, bleeding, pain, perforation, and possibly pregnancy.

Insertion Procedure

Proceed with insertion only after completing the above steps and ascertaining that the patient is appropriate for Mirena. Ensure use of aseptic technique throughout the entire procedure.

Step 1–Opening of the package

- Open the package (Figure 1). The contents of the package are sterile.

Figure 1: Opening the Mirena Package

- Using sterile gloves lift the handle of the sterile inserter and remove from the sterile package.

Step 2–Load Mirena into the insertion tube

- Push the slider forward as far as possible in the direction of the arrow thereby moving the insertion tube over the Mirena T-body to load Mirena into the insertion tube (Figure 2). The tips of the arms will meet to form a rounded end that extends slightly beyond the insertion tube.

Figure 2: Move slider all the way to the forward position to load Mirena

- Maintain forward pressure with your thumb or forefinger on the slider. DO NOT move the slider downward at this time as this may prematurely release the threads of Mirena. Once the slider is moved below the mark, Mirena cannot be re-loaded.

Step 3–Setting the Flange

- Holding the slider in this forward position, set the upper edge of the flange to correspond to the uterine depth (in centimeters) measured during sounding (Figure 3).

Figure 3: Setting the flange

Step 4–Mirena is now ready to be inserted

- Continue holding the slider in this forward position. Advance the inserter through the cervix until the flange is approximately 1.5–2 cm from the cervix and then pause (Figure 4).

Figure 4: Advancing insertion tube until flange is 1.5 to 2 cm from the cervix

Do not force the inserter. If necessary, dilate the cervical canal.

Step 5–Open the arms

While holding the inserter steady, move the slider down to the mark to release the arms of Mirena (Figure 5). Wait 10 seconds for the horizontal arms to open completely.

Figure 5: Move the slider back to the mark to release and open the arms

Step 6–Advance to fundal position

- Advance the inserter gently towards the fundus of the uterus until the flange touches the cervix. If you encounter fundal resistance do not continue to advance. Mirena is now in the fundal position (Figure 6). Fundal positioning of Mirena is important to prevent expulsion.

Figure 6: Move Mirena into the fundal position

Step 7–Release Mirena and withdraw the inserter

- Holding the entire inserter firmly in place, release Mirena by moving the slider all the way down (Figure 7).

Figure 7: Move the slider all the way down to release Mirena from the insertion tube

- Continue to hold the slider all the way down while you slowly and gently withdraw the inserter from the uterus.
- Using a sharp, curved scissor, cut the threads perpendicular, leaving about 3 cm visible outside of the cervix [cutting threads at an angle may leave sharp ends (Figure 8)]. Do not apply tension or pull on the threads when cutting to prevent displacing Mirena.

Figure 8: Cutting the threads

Mirena insertion is now complete. Prescribe analgesics, if indicated. Record the Mirena lot number in the patient records.

Important information to consider during or after insertion

- If you suspect that Mirena is not in the correct position, check placement (for example, using transvaginal ultrasound). Remove Mirena if it is not positioned completely within the uterus. Do not reinsert a removed Mirena.
- If there is clinical concern, exceptional pain or bleeding during or after insertion, take appropriate steps (such as physical examination and ultrasound) immediately to exclude perforation.

2.3 Patient Follow-up

Reexamine and evaluate patients 4 to 6 weeks after insertion and once a year thereafter, or more frequently if clinically indicated.

2.4 Removal of Mirena

Timing of Removal

- For contraception, remove Mirena by the end of the eighth year and replace at the time of removal with a new Mirena if continued use is desired. Replace Mirena by the end of the fifth year if continued treatment of heavy menstrual bleeding is needed.
- If pregnancy is not desired, remove Mirena during the first 7 days of the menstrual cycle, provided the woman is still experiencing regular menses. If removal will occur at other times during the cycle, or the woman does not experience regular menses, she is at risk of pregnancy; start a new contraceptive method a week prior to removal for these women. [See Dosage and Administration (2.5).]

Tools for Removal

Preparation

- Gloves
- Speculum

Procedure

- Sterile forceps

Removal Procedure

- Remove Mirena by applying gentle traction on the threads with forceps. (Figure 9).

Figure 9: Removal of Mirena

- If the threads are not visible, determine location of Mirena by ultrasound [see Warnings and Precautions (5.10)].
- If Mirena is found to be in the uterine cavity on ultrasound exam, it may be removed using a narrow forceps, such as an alligator forceps. This may require dilation of the cervical canal. After removal of Mirena, examine the system to ensure that it is intact. The hormone cylinder may slide over and cover the horizontal arms, giving the appearance of missing arms. This situation generally does not require further intervention once the system is verified to be intact.
- If unable to remove with gentle traction, determine Mirena location and exclude perforation by ultrasound or other imaging [see Warnings and Precautions (5.10)].
- Removal may be associated with:
  - pain and/or bleeding, vasovagal reactions (for example, syncope, bradycardia) or seizure, especially in patients with a predisposition to these conditions.
  - breakage or embedment of Mirena in the myometrium that can make removal difficult [see Warnings and Precautions (5.5)]. Analgesia, paracervical anesthesia, cervical dilation, alligator forceps or other grasping instrument, or hysteroscopy may be used to assist in removal.

2.5 Continuation of Contraception after Removal

- If pregnancy is not desired and if a woman wishes to continue using Mirena, a new system can be inserted immediately after removal any time during the cycle.
- If a patient with regular cycles wants to start a different contraceptive method, time removal and initiation of the new method to ensure continuous contraception. Either remove Mirena during the first 7 days of the menstrual cycle and start the new method immediately thereafter or start the new method at least 7 days prior to removing Mirena if removal is to occur at other times during the cycle.
- If a patient with irregular cycles or amenorrhea wants to start a different contraceptive method, start the new method at least 7 days before removal.

3 DOSAGE FORMS AND STRENGTHS

Mirena is a LNG-releasing IUS (a type of intrauterine device, or IUD) consisting of a T-shaped polyethylene frame with a steroid reservoir containing a total of 52 mg LNG.

4 CONTRAINDICATIONS

The use of Mirena is contraindicated when one or more of the following conditions exist:

- Pregnancy or suspicion of pregnancy [see Warnings and Precautions (5.2), Use in Specific Populations (8.1)]
- For use as post-coital contraception (emergency contraception)
- Congenital or acquired uterine anomaly including fibroids, that distorts the uterine cavity
- Acute pelvic inflammatory disease (PID) or a history of PID unless there has been a subsequent intrauterine pregnancy [see Warnings and Precautions (5.4)]
- Postpartum endometritis or infected abortion in the past 3 months
- Known or suspected uterine or cervical malignancy
- Known or suspected breast cancer or other progestin-sensitive cancer, now or in the past
- Uterine bleeding of unknown etiology
- Untreated acute cervicitis or vaginitis, including bacterial vaginosis or other lower genital tract infections until infection is controlled
- Acute liver disease or liver tumor (benign or malignant)
- Conditions associated with increased susceptibility to pelvic infections [see Warnings and Precautions (5.4)]
- A previously inserted intrauterine device (IUD) that has not been removed
- Hypersensitivity to any component of this product [see Adverse Reactions (6.2) and Description (11.1)]

5 WARNINGS AND PRECAUTIONS

5.1 Risk of Ectopic Pregnancy

Evaluate women for ectopic pregnancy if they become pregnant with Mirena in place because the likelihood of a pregnancy being ectopic is increased with Mirena. Approximately one-half of pregnancies that occur with Mirena in place are likely to be ectopic. Also consider the possibility of ectopic pregnancy in the case of lower abdominal pain, especially in association with missed menses or if an amenorrheic woman starts bleeding.

The incidence of ectopic pregnancy in clinical trials with Mirena, which excluded women with a history of ectopic pregnancy, was approximately 0.1% per year. The risk of ectopic pregnancy, in women who have a history of ectopic pregnancy and use Mirena is unknown. Women with a previous history of ectopic pregnancy, tubal surgery or pelvic infection carry a higher risk of ectopic pregnancy. Ectopic pregnancy may result in loss of fertility.

5.2 Risks with Intrauterine Pregnancy

If pregnancy occurs while using Mirena, remove Mirena because leaving it in place may increase the risk of spontaneous abortion and preterm labor. Removal of Mirena or probing of the uterus may also result in spontaneous abortion. In the event of an intrauterine pregnancy with Mirena, consider the following:

Septic abortion

In patients becoming pregnant with an IUS in place, septic abortion - with septicemia, septic shock, and death - may occur.

Continuation of pregnancy

If a woman becomes pregnant with Mirena in place and if Mirena cannot be removed or the woman chooses not to have it removed, warn her that failure to remove Mirena increases the risk of miscarriage, sepsis, premature labor and premature delivery. Advise her of isolated reports of virilization of the female fetus following local exposure to LNG during pregnancy with an LNG IUS in place [see Use in Specific Populations (8.1)]. Follow her pregnancy closely and advise her to report immediately any symptom that suggests complications of the pregnancy.

5.3 Sepsis

Severe infection or sepsis, including Group A streptococcal sepsis (GAS), have been reported following insertion of Mirena. In some cases, severe pain occurred within hours of insertion followed by sepsis within days. Because death from GAS is more likely if treatment is delayed, it is important to be aware of these rare but serious infections. Aseptic technique during insertion of Mirena is essential in order to minimize serious infections such as GAS.

5.4 Pelvic Infection

Promptly examine users with complaints of lower abdominal or pelvic pain, odorous discharge, unexplained bleeding, fever, genital lesions or sores. Remove Mirena in cases of recurrent endometritis or PID, or if an acute pelvic infection is severe or does not respond to treatment.

Pelvic Inflammatory Disease (PID)

Mirena is contraindicated in the presence of known or suspected PID or in women with a history of PID unless there has been a subsequent intrauterine pregnancy [see Contraindications (4)]. IUDs have been associated with an increased risk of PID, most likely due to organisms being introduced into the uterus during insertion. In clinical trials, total combined upper genital infections were reported in 3.5% of Mirena users. More specifically, endometritis was reported in 2.1%, PID in 0.6%, and all other upper genital infections in ≤0.5% of women overall. These infections occurred more frequently within the first year. In a clinical trial with other IUDs^1 and a clinical trial with an IUD similar to Mirena, the highest rate occurred within the first month after insertion.

Women at increased risk for PID

PID is often associated with a sexually transmitted infection (STI), and Mirena does not protect against STI. The risk of PID is greater for women who have multiple sexual partners, and also for women whose sexual partner(s) have multiple sexual partners. Women who have had PID are at increased risk for a recurrence or re-infection. In particular, ascertain whether the woman is at increased risk of infection (for example, leukemia, acquired immune deficiency syndrome [AIDS], intravenous drug abuse).

Subclinical PID

PID may be asymptomatic but still result in tubal damage and its sequelae.

Treatment of PID

Following a diagnosis of PID, or suspected PID, bacteriologic specimens should be obtained, and antibiotic therapy should be initiated promptly. Removal of Mirena after initiation of antibiotic therapy is usually appropriate.^1

Actinomycosis

Actinomycosis has been associated with IUDs. Remove Mirena from symptomatic women and treat with antibiotics. The significance of actinomyces-like organisms on Pap smear in an asymptomatic IUD user is unknown, and so this finding alone does not always require Mirena removal and treatment. When possible, confirm a Pap smear diagnosis with cultures.

5.5 Perforation

Perforation (total or partial, including penetration/embedment of Mirena in the uterine wall or cervix) may occur most often during insertion, although the perforation may not be detected until sometime later. The incidence of perforation during clinical trials, which excluded breast-feeding women, was < 0.1%.

The risk of uterine perforation is increased in women who have recently given birth, and in women who are breastfeeding at the time of insertion. In a large postmarketing safety study conducted in the US, the risk of uterine perforation was highest when insertion occurred within ≤ 6 weeks postpartum, and also higher with breastfeeding at the time of insertion [see Adverse Reactions (6.2)].

The risk of perforation may be increased if Mirena is inserted when the uterus is fixed, retroverted or not completely involuted.

If perforation occurs, locate and remove Mirena. Surgery may be required. Delayed detection or removal of Mirena in case of perforation may result in migration outside the uterine cavity, adhesions, peritonitis, intestinal perforations, intestinal obstruction, abscesses and erosion of adjacent viscera. In addition, perforation may reduce contraceptive efficacy and result in pregnancy.

5.6 Expulsion

Partial or complete expulsion of Mirena may occur resulting in the loss of efficacy. Expulsion may be associated with symptoms of bleeding or pain, or it may be asymptomatic and go unnoticed. Mirena typically decreases menstrual bleeding over time; therefore, an increase of menstrual bleeding may be indicative of an expulsion. Consider further diagnostic imaging, such as x-ray, if expulsion is suspected based on ultrasound [see Warnings and Precautions (5.10)]. In clinical trials, a 4.5% expulsion rate was reported over the 5-year study duration.

The risk of expulsion is increased with insertions immediately after delivery and appears to be increased with insertion after second-trimester abortion based on limited data. In a large postmarketing safety study conducted in the US, the risk of expulsion was lower with breastfeeding status [see Adverse Reactions (6.2)].

Remove a partially expelled Mirena. If expulsion has occurred, a new Mirena can be inserted any time the provider can be reasonably certain the woman is not pregnant.

5.7 Ovarian Cysts

Because the contraceptive effect of Mirena is mainly due to its local effects within the uterus, ovulatory cycles with follicular rupture usually occur in women of fertile age using Mirena. Ovarian cysts have been reported in approximately 8% of women using Mirena. Most cysts are asymptomatic, although some may be accompanied by pelvic pain or dyspareunia.

In most cases the ovarian cysts disappear spontaneously during two to three months observation. Evaluate persistent ovarian cysts. Surgical intervention is not usually required.

5.8 Bleeding Pattern Alterations

Mirena can alter the bleeding pattern and result in spotting, irregular bleeding, heavy bleeding, oligomenorrhea and amenorrhea. During the first 3–6 months of Mirena use, the number of bleeding and spotting days may be higher and bleeding patterns may be irregular. Thereafter the number of bleeding and spotting days usually decreases but bleeding may remain irregular. If bleeding irregularities develop during prolonged treatment, appropriate diagnostic measures should be taken to rule out endometrial pathology.

Amenorrhea develops in approximately 20% of Mirena users by one year.

If a significant change in bleeding develops during prolonged use, take appropriate diagnostic measures to rule out endometrial pathology. Consider the possibility of pregnancy if menstruation does not occur within six weeks of the onset of previous menstruation. Once pregnancy has been excluded, repeated pregnancy tests are generally not necessary in amenorrheic women unless indicated, for example, by other signs of pregnancy or by pelvic pain [see Clinical Studies (14.1)].

In most women with heavy menstrual bleeding, the number of bleeding and spotting days may also increase during the initial months of therapy but usually decrease with continued use; the volume of blood loss per cycle progressively becomes reduced [see Clinical Studies (14.2)].

5.9 Breast Cancer

Women who currently have or have had breast cancer, or have a suspicion of breast cancer, should not use hormonal contraception, including Mirena, because some breast cancers are hormone-sensitive [see Contraindications (4)].

Spontaneous reports of breast cancer have been received during postmarketing experience with Mirena. Observational studies of the risk of breast cancer with use of a LNG-releasing IUS do not provide conclusive evidence of increased risk.

5.10 Clinical Considerations for Use and Removal

Use Mirena with caution after careful assessment if any of the following conditions exist, and consider removal of the system if any of them arise during use:

- Coagulopathy or use of anticoagulants
- Migraine, focal migraine with asymmetrical visual loss or other symptoms indicating transient cerebral ischemia
- Exceptionally severe headache
- Marked increase of blood pressure
- Severe arterial disease such as stroke or myocardial infarction

In addition, consider removing Mirena if any of the following conditions arise during use [see Contraindications (4)]:

- Uterine or cervical malignancy
- Jaundice

If the threads are not visible or are significantly shortened, they may have broken or retracted into the cervical canal or uterus. Consider the possibility that the system may have been displaced (for example, expelled or perforated the uterus) [see Warnings and Precautions (5.5, 5.6)]. Exclude pregnancy and verify the location of Mirena, for example, by sonography, X-ray, or by gentle exploration of the cervical canal with a suitable instrument. If Mirena is displaced, remove it. A new Mirena may be inserted at that time or during the next menses if it is certain that conception has not occurred. If Mirena is in place with no evidence of perforation, no intervention is indicated.

6 ADVERSE REACTIONS

The following serious or otherwise important adverse reactions are discussed in elsewhere in the labeling:

- Ectopic Pregnancy [see Warnings and Precautions (5.1)]
- Intrauterine Pregnancy [see Warnings and Precautions (5.2)]
- Group A Streptococcal Sepsis (GAS) [see Warnings and Precautions (5.3)]
- Pelvic Inflammatory Disease [see Warnings and Precautions (5.4)]
- Perforation [see Warnings and Precautions (5.5)]
- Expulsion [see Warnings and Precautions (5.6)]
- Ovarian Cysts [see Warnings and Precautions (5.7)]
- Bleeding Pattern Alterations [see Warnings and Precautions (5.8)]

6.1 Clinical Trials Experience

Because clinical trials are conducted under widely varying conditions, adverse reaction rates observed in the clinical trials of a drug cannot be directly compared to rates in the clinical trials of another drug and may not reflect the rates observed in clinical practice.

The data provided in Table 2 reflect the experience with the use of Mirena in the adequate and well-controlled studies as well as in the supportive and uncontrolled studies for contraception and heavy menstrual bleeding (n=5,091). The data cover more than 12,101 women-years of exposure up to 5 years of use, mainly in the contraception studies (11,761 women-years). The frequencies of reported adverse drug reactions represent crude incidences.

The most common adverse reactions (≥10% users) are alterations of menstrual bleeding patterns [including unscheduled uterine bleeding (31.9%), decreased uterine bleeding (23.4%), increased scheduled uterine bleeding (11.9%), and female genital tract bleeding (3.5%)], abdominal/pelvic pain (22.6%), amenorrhea (18.4%), headache/migraine (16.3%), genital discharge (14.9%), and vulvovaginitis (10.5%). Adverse reactions reported in ≥ 5% of users are shown in Table 2.

Table 2: Adverse Reactions ≥ 5% Reported in Clinical Trials with Mirena
System Organ Class | Adverse Reactions | % (N= 5,091)
Reproductive system and breast disorders | alteration of menstrual bleeding pattern, including:; unscheduled uterine bleeding; decreased uterine bleeding; increased scheduled uterine bleeding; female genital tract bleeding | 31.9; 23.4; 11.9; 3.5
 | amenorrhea | 18.4
 | genital discharge | 14.9
 | vulvovaginitis | 10.5
 | breast pain | 8.5
 | benign ovarian cyst and associated complications | 7.5
 | dysmenorrhea | 6.4
Gastrointestinal disorders | abdominal/pelvic pain | 22.6
Nervous system disorders | headache/migraine | 16.3
Musculoskeletal and connective tissue disorders | back pain | 7.9
Skin and subcutaneous tissue disorders | acne | 6.8
Psychiatric disorders | depression/depressive mood | 6.4

Other adverse reactions occurring in <5% of subjects include alopecia, (partial and complete) device expulsion, hirsutism, nausea, and PID/endometritis.

A separate study with 362 women who have used Mirena for more than 5 years showed a consistent adverse reaction profile in Years 6 through 8 as shown in Table 2. By the end of Year 8 of use, amenorrhea and infrequent bleeding are experienced by 34% and 26% of users, respectively; irregular bleeding occurs in 10%, frequent bleeding in 3%, and prolonged bleeding in 3% of users. In this study, 9% of women reported the adverse event of weight gain; it is unknown if the weight gain was caused by Mirena.

6.2 Postmarketing Experience

Adverse Reactions from Postmarketing Spontaneous Reports

The following adverse reactions have been identified during post approval use of Mirena. Because these reactions are reported voluntarily from a population of uncertain size, it is not always possible to reliably estimate their frequency or establish a causal relationship to drug exposure.

- Arterial thrombotic and venous thromboembolic events, including cases of pulmonary embolism, deep vein thrombosis and stroke
- Device breakage
- Hypersensitivity (including rash, urticaria and angioedema)
- Increased blood pressure

Reported Adverse Reactions from Postmarketing Studies

Assessment of Perforation and Expulsion of Intrauterine Devices (APEX IUD) Study

APEX IUD was a large US retrospective cohort study to assess the impact of breastfeeding and timing of postpartum IUD insertion on uterine perforation and IUD expulsion. The analyses included a total of 326,658 insertions, 30% (97,824 insertions) of which were performed in women with a delivery in the previous 12 months. For insertions performed in women who had delivered ≤ 52 weeks before IUD insertion, the majority of postpartum insertions, 57.3% (56,047 insertions) occurred between 6 and 14 weeks postpartum. Breastfeeding data were available in 94,817 insertions performed in women 52 weeks or less after delivery.

The study results indicated that the risk of uterine perforation was highest in women with IUD insertion ≤ 6 weeks postpartum. Immediate postpartum insertion (0–3 days) findings are limited due to the relatively small number of insertions occurring within this time interval. Women who were breastfeeding at the time of insertion were at 33% higher risk of perforation (adjusted hazard ratio [HR]=1.33, 95% confidence interval [CI]: 1.07–1.64) compared to women who were not breastfeeding at the time of insertion. Progressively lower risk of uterine perforation was observed in postpartum time windows beyond 6 weeks, in both breastfeeding and not breastfeeding women. Table 3 presents the uterine perforation rates for LNG IUS stratified by breastfeeding status and postpartum interval.

Table 3: Uterine Perforation1 rates for LNG IUS, by Breastfeeding Status and Postpartum Interval
 | Breastfeeding at time of insertion |  | Not breastfeeding at time of insertion
Postpartum interval at time of insertion | Number of events/ insertions | Uterine perforation rate per 1,000 insertions | Number of events/ insertions | Uterine perforation rate per 1,000 insertions
0 to 3 days | 8/1,896 | 4.22 | 0/277 | 0.00
4 days to ≤ 6 weeks | 120/10,735 | 11.18 | 28/2,377 | 11.78
> 6 to ≤ 14 weeks | 268/29,677 | 9.03 | 80/12,011 | 6.66
> 14 to ≤ 52 weeks | 43/6,139 | 7.00 | 22/9,089 | 2.42
> 52 weeks or no delivery | no data available |  | 243/184,733 | 1.32

Risk of expulsion was variable over the postpartum intervals through 52 weeks. Women who were breastfeeding were at 28% lower risk of IUD expulsion (adjusted HR=0.72, 95% CI: 0.64-0.80) compared to women who were not breastfeeding at time of insertion. Table 4 presents the IUD expulsion rates for LNG IUS stratified by breastfeeding status and postpartum interval.

Table 4: Expulsion1 Rates for LNG IUS, by Breastfeeding Status and Postpartum Interval
 | Breastfeeding at time of insertion |  | Not breastfeeding at time of insertion
Postpartum interval at time of insertion | Number of events/ insertions | Expulsion rate per 1,000 insertions | Number of events/ insertions | Expulsion rate per 1,000 insertions
0 to 3 days | 187/1,896 | 98.63 | 12/277 | 43.32
4 days to ≤ 6 weeks | 185/10,735 | 17.23 | 52/2,377 | 21.88
> 6 to ≤ 14 weeks | 421/29,677 | 14.19 | 306/12,011 | 25.48
> 14 to ≤ 52 weeks | 120/6,139 | 19.55 | 273/9,089 | 30.04
> 52 weeks or no delivery | no data available |  | 5,481/184,733 | 29.67

^1Expulsion includes both complete and partial expulsion

7 DRUG INTERACTIONS

No drug-drug interaction studies have been conducted with Mirena.

Drugs or herbal products that induce or inhibit LNG metabolizing enzymes, including CYP3A4, may decrease or increase, respectively, the serum concentrations of LNG during the use of Mirena. However, the contraceptive effect of Mirena is mediated via the direct release of LNG into the uterine cavity and is unlikely to be affected by drug interactions via enzyme induction or inhibition.

8 USE IN SPECIFIC POPULATIONS

8.1 Pregnancy

Risk Summary

The use of Mirena is contraindicated in pregnancy or with a suspected pregnancy and Mirena may cause adverse pregnancy outcomes [see Contraindications (4), Warnings and Precautions (5.1, 5.2)]. If a woman becomes pregnant with Mirena in place, the likelihood of ectopic pregnancy is increased and there is an increased risk of miscarriage, sepsis, premature labor, and premature delivery. Remove Mirena, if possible, if pregnancy occurs in a woman using Mirena. If Mirena cannot be removed, follow the pregnancy closely [see Warnings and Precautions (5.1, 5.2)].

There have been isolated cases of virilization of the external genitalia of the female fetus following local exposure to LNG during pregnancy with an LNG IUS in place.

8.2 Lactation

Risk Summary

Published studies report the presence of LNG in human milk. Small amounts of progestins (approximately 0.1% of the total maternal doses) were detected in the breast milk of nursing mothers who used Mirena, resulting in exposure of LNG to the breastfed infants. There are no reports of adverse effects in breastfed infants with maternal use of progestin-only contraceptives. Isolated cases of decreased milk production have been reported with Mirena. The developmental and health benefits of breastfeeding should be considered along with the mother's clinical need for Mirena and any potential adverse effects on the breastfed child from Mirena or from the underlying maternal condition.

8.3 Females and Males of Reproductive Potential

Return to Fertility After Discontinuing Mirena

In two studies, return to fertility was investigated in a total of 229 women who desired pregnancy after study discontinuation and provided follow-up information. The probability to conceive within 12 months after removal of Mirena was approximately 80%.

8.4 Pediatric Use

Safety and efficacy of Mirena have been established in women of reproductive age. Efficacy is expected to be the same for postpubertal females under the age of 18 as for users 18 years and older. Use of this product before menarche is not indicated.

8.5 Geriatric Use

Mirena has not been studied in women over age 65 and is not approved for use in this population.

11 DESCRIPTION

Mirena (levonorgestrel-releasing intrauterine system) contains 52 mg of LNG, a progestin, and is intended to provide an initial release rate of LNG of approximately 21 mcg/day after 24 days.

Levonorgestrel USP, (-)-13-Ethyl-17-hydroxy-18,19-dinor-17α-pregn-4-en-20-yn-3-one, the active ingredient in Mirena, has a molecular weight of 312.4, a molecular formula of C21H28O2, and the following structural formula:

11.1 Mirena

Mirena consists of a T-shaped polyethylene frame (T-body) with a steroid reservoir (hormone elastomer core) around the vertical stem. The white T-body has a loop at one end of the vertical stem and two horizontal arms at the other end. The reservoir consists of a white or almost white cylinder, made of a mixture of LNG and silicone (polydimethylsiloxane), containing a total of 52 mg LNG. The reservoir is covered by a semi-opaque silicone membrane, composed of polydimethylsiloxane and colloidal silica. The T-body is 32 mm in both the horizontal and vertical directions. The polyethylene of the T-body is compounded with barium sulfate, which makes it radiopaque. A monofilament brown polyethylene removal thread is attached to a loop at the end of the vertical stem of the T-body. The polyethylene of the removal thread contains iron oxide as a colorant (see Figure 10).

The components of Mirena, including its packaging, are not manufactured using natural rubber latex.

Figure 10: Mirena

11.2 Inserter

Mirena is packaged sterile within an inserter. The inserter (Figure 11), which is used for insertion of Mirena into the uterine cavity, consists of a symmetric two-sided body and slider that are integrated with flange, lock, pre-bent insertion tube and plunger. The outer diameter of the insertion tube is 4.4 mm. The vertical stem of Mirena is loaded in the insertion tube at the tip of the inserter. The arms are pre-aligned in the horizontal position. The removal threads are contained within the insertion tube and handle. Once Mirena has been placed, the inserter is discarded.

Figure 11: Diagram of Inserter

12 CLINICAL PHARMACOLOGY

12.1 Mechanism of Action

The local mechanism by which continuously released LNG contributes to the contraceptive effectiveness of Mirena has not been conclusively demonstrated. Studies of Mirena and similar LNG IUS prototypes have suggested several mechanisms that prevent pregnancy: thickening of cervical mucus preventing passage of sperm into the uterus, inhibition of sperm capacitation or survival, and alteration of the endometrium.

12.2 Pharmacodynamics

Mirena has mainly local progestogenic effects in the uterine cavity. The local concentrations of LNG lead to morphological changes including stromal pseudodecidualization, glandular atrophy, a leukocytic infiltration and a decrease in glandular and stromal mitoses.

Ovulation is inhibited in some women using Mirena. In a 1-year study, approximately 45% of menstrual cycles were ovulatory, and in another study after 4 years, 75% of cycles were ovulatory.

12.3 Pharmacokinetics

Absorption

Low doses of LNG are administered into the uterine cavity with the Mirena intrauterine delivery system.

Estimated in vivo release rates for different points in time are provided in Table 5.

Table 5: Estimated in vivo release rates for Mirena:
Time | Estimated in vivo release rate [μg/day] (rounded)
24 days after insertion | 21
60 days after insertion | 21
1 year after insertion | 19
3 years after insertion | 14
5 years after insertion | 11
6 years after insertion | 9
7 years after insertion | 8
8 years after insertion | 7
Average over 1st year | 20
Average over 3 years | 18
Average over 5 years | 15
Average over 8 years | 13

After insertion of Mirena, LNG is detectable in serum/plasma after 1 hour. The maximum concentration is reached within 2 weeks after insertion and amounts to about 180 ng/L (CV 38%). In correspondence with the declining release rate, the geometric mean serum/plasma concentration of levonorgestrel declines continuously:

Table 6: Estimated Total LNG Mean Plasma Concentrations
Time after insertion | Total LNG plasma concentrations [ng/L] (geometric CV%)
24 days | 175 (37.6)
2 months | 169 (37.1)
1 year | 159 (37.4)
3 years | 139 (37.8)
5 years | 123 (38.2)
8 years | 100 (39.9)

Distribution

LNG is bound non-specifically to serum albumin and specifically to the Sex hormone-binding globulin (SHBG.) Less than 2% of the circulating LNG is present as free steroid. Levonorgestrel binds with high affinity to SHBG. Accordingly, changes in the concentration of SHBG in serum result in an increase (at higher SHBG concentrations) or in a decrease (at lower SHBG concentrations) of the total levonorgestrel concentration in serum. The concentration of SHBG declined on average by about 20% during the two months after insertion of Mirena and remained stable during thereafter, increasing only slightly until the end of the 8 years of use.

The apparent volume of distribution of LNG is reported to be approximately 1.8 L/kg.

Elimination

Following intravenous administration of 0.09 mg LNG to healthy volunteers, the total clearance of LNG is approximately 1 mL/min/kg and the elimination half-life is approximately 20 hours. Metabolic clearance rates may differ among individuals by several-fold, and this may account in part for wide individual variations in LNG concentrations seen in individuals using LNG–containing contraceptive products.

Metabolism

Following absorption, LNG is extensively metabolized. The most important metabolic pathways are the reduction of the Δ4-3-oxo group and hydroxylations at positions 2α, 1β and 16β, followed by conjugation. Significant amounts of conjugated and unconjugated 3α, 5β-tetra-hydrolevonorgestrel are also present in serum, along with much smaller amounts of 3α, 5α-tetrahydrolevonorgestrel and 16β-hydroxylevonorgestrel. CYP3A4 is the main enzyme involved in the oxidative metabolism of LNG.

Excretion

LNG and its phase I metabolites are excreted primarily as glucuronide conjugates. About 45% of LNG and its metabolites are excreted in the urine and about 32% are excreted in feces, mostly as glucuronide conjugates.

Specific Populations

Pediatric: Safety and efficacy of Mirena have been established in women of reproductive age. Use of this product before menarche is not indicated.

Geriatric: Mirena has not been studied in women over age 65 and is not currently approved for use in this population.

Race: No studies have evaluated the effect of race on the pharmacokinetics of Mirena.

Hepatic Impairment: No studies were conducted to evaluate the effect of hepatic disease on the disposition of Mirena.

Renal Impairment: No formal studies were conducted to evaluate the effect of renal disease on the disposition of Mirena.

Drug-Drug Interactions

No drug-drug interaction studies were conducted with Mirena [see Drug Interactions (7)].

13 NONCLINICAL TOXICOLOGY

13.1 Carcinogenesis, Mutagenesis, Impairment of Fertility

[See Warnings and Precautions (5.9)]

14 CLINICAL STUDIES

14.1 Clinical Trials on Contraception

The safety and effectiveness of Mirena was studied in two clinical trials in Finland and Sweden. In these trials, 1,169 women 18 to 35 years of age at enrollment used Mirena for up to 5 years, for a total of 45,000 women-months of exposure. Of these, 5.6% (66) were nulliparous women. Subjects had previously been pregnant, had no history of ectopic pregnancy, had no history of pelvic inflammatory disease over the preceding 12 months, were predominantly White, and over 70% of the subjects had previously used IUDs (intrauterine devices). The reported 12-month pregnancy rates were less than or equal to 0.2 per 100 women (0.2%) and the cumulative 5-year pregnancy rate was approximately 0.7 per 100 women (0.7%).

The contraceptive efficacy of Mirena during extended use beyond 5 years was studied in the Mirena Extension Trial (NCT02985541), a multi-center, open-label, uncontrolled study conducted in the United States. The trial enrolled women 18 to 35 years of age who had been using Mirena for not less than 4.5 years and not more than 5 years at enrollment. The population consisted of 362 women using Mirena. Of these 47.2% were nulliparous. The women were predominantly White (75.4%); 14.1% of the women were Black/African American, and 2.5% were Asian; 11.3 % were Hispanic. The weight range was 38.5–163.5 kg (mean weight: 75.6 kg) and mean BMI was 27.9 kg/m^2 (range: 15.4–57.7 kg/m^2).

The pregnancy rate calculated as the Pearl Index (PI) was the primary efficacy endpoint used to assess contraceptive efficacy. The PI was based on 28-day equivalent exposure cycles; evaluable cycles excluded those in which back-up contraception was used unless a pregnancy occurred in that cycle. The PI for the 6th year of use based on the 1 pregnancy that occurred during Year 6 and within 7 days after Mirena removal or expulsion and 3,870 evaluable cycles was 0.34 with a 95% upper confidence limit of 1.88, and the PI for the 7th year of use based on the 1 pregnancy that occurred during Year 7 and within 7 days after Mirena removal or expulsion and 3,232 evaluable cycles was 0.40 with a 95% upper confidence limit of 2.25. The PI for the 8th year of use based on no pregnancies occurring during Year 8 and within 7 days after Mirena removal or expulsion and 2,534 evaluable cycles was 0.00 with a 95% upper confidence limit of 1.90.

The cumulative 3-year pregnancy rate for Years 6, 7 and 8 was estimated by the Kaplan-Meier method. Based on 2 pregnancies (1 in Year 6 and 1 in Year 7) and 10,216 exposure cycles, the cumulative pregnancy rate at the end of the 3-year period of extended use (Years 6, 7 and 8) was 0.68% with a 95% upper confidence limit of 2.71%.

14.2 Clinical Trial on Heavy Menstrual Bleeding

The efficacy of Mirena in the treatment of heavy menstrual bleeding was studied in a randomized, open-label, active-control, parallel-group trial comparing Mirena (n=79) to an approved therapy, medroxyprogesterone acetate (MPA) (n=81), over 6 cycles. The subjects included reproductive-aged women in good health, with no contraindications to the drug products and with confirmed heavy menstrual bleeding (≥ 80 mL menstrual blood loss [MBL]) determined using the alkaline hematin method. Excluded were women with organic or systemic conditions that may cause heavy uterine bleeding (except small fibroids, with total volume not > 5 mL). Treatment with Mirena showed a statistically significantly greater reduction in MBL (see Figure 12) and a statistically significantly greater number of subjects with successful treatment (see Figure 13). Successful treatment was defined as proportion of subjects with (1) end-of-study MBL < 80 mL and (2) a ≥ 50% decrease in MBL from baseline to end-of-study.

Figure 12: Median Menstrual Blood Loss (MBL) by Time and Treatment
Figure 13: Proportion of Subjects with Successful Treatment

15 REFERENCES

^1 http://www.cdc.gov/std/tg2015/pid.htm. Accessed August 22, 2016.

16 HOW SUPPLIED/STORAGE AND HANDLING

Mirena (levonorgestrel-releasing intrauterine system), containing a total of 52 mg LNG, is available in a carton of one sterile unit NDC# 50419-423-01.

Mirena is supplied sterile. Mirena is sterilized with ethylene oxide. Do not resterilize. For single use only. Do not use if the inner package is damaged or open. Insert before the end of the month shown on the label.

Store at 25°C (77°F); with excursions permitted between 15–30°C (59–86°F) [see USP Controlled Room Temperature].

17 PATIENT COUNSELING INFORMATION

Advise the patient to read the FDA-approved patient labeling (Patient Information)

- Sexually Transmitted Infections: Advise the patient that this product does not protect against HIV infection (AIDS) and other sexually transmitted infections (STIs).
- Risk of Ectopic Pregnancy: Advise the patient about the risks of ectopic pregnancy, including the loss of fertility. Teach her to recognize and report to her healthcare provider promptly any symptoms of ectopic pregnancy. [See Warnings and Precautions (5.1).]
- Risks of Intrauterine Pregnancy: Advise the patient to contact her healthcare provider if she thinks she might be pregnant. Inform the patient about the risks of intrauterine pregnancy while using Mirena, including the risks of leaving Mirena in place and the risks of removing Mirena or probing of the uterus. If Mirena cannot be removed in a pregnant patient, advise her to report immediately any symptom that suggests complications of the pregnancy. Advise her of isolated reports of virilization of the female fetus following local exposure to LNG during pregnancy with an LNG IUS in place. [See Warnings and Precautions (5.2) and Use in Special Populations (8.1).]
- Sepsis: Counsel the patient that severe infection or sepsis, including Group A streptococcal sepsis (GAS), can occur within the first few days after Mirena is inserted. Instruct her to contact a healthcare provider immediately if she develops severe pain or fever shortly after Mirena is inserted. [See Warnings and Precautions (5.3).]
- Pelvic Infection: Advise the patient about the possibility of pelvic infections, including PID, and that these infections can cause tubal damage leading to ectopic pregnancy or infertility, or infrequently can necessitate hysterectomy, or cause death. Teach patients to recognize and report to their healthcare provider promptly any symptoms of pelvic infection. These symptoms include development of menstrual disorders (prolonged or heavy bleeding), unusual vaginal discharge, abdominal or pelvic pain or tenderness, dyspareunia, chills, and fever. [See Warnings and Precautions (5.4).]
- Perforation and Expulsion: Advise the patient that the IUS may be expelled from or perforate the uterus and instruct her on how she can check that the threads still protrude from the cervix. Inform her that excessive pain or vaginal bleeding during Mirena placement, worsening pain or bleeding after placement, or the inability to feel Mirena strings may occur with Mirena perforation and expulsion. Caution her not to pull on the threads and displace Mirena. Inform her that there is no contraceptive protection if Mirena is displaced or expelled. Instruct the patient to contact her healthcare provider if she cannot feel the threads and to avoid intercourse or use a non-hormonal back-up birth control (such as condoms or spermicide) until the location of Mirena has been confirmed. Advise her that if perforation occurs, Mirena will have to be located and removed; surgery may be required. [See Warnings and Precautions (5.5, 5.6, 5.10).]
- Ovarian Cysts: Advise the patient regarding the risk of ovarian cysts and that cysts can cause clinical symptoms including pelvic pain, abdominal pain or dyspareunia. Advise the patient to contact her healthcare provider if she experiences these symptoms. [See Warnings and Precautions (5.7).]
- Bleeding Pattern Alterations: Advise the patient that irregular or prolonged bleeding and spotting, and/or cramps may occur during the first few weeks after insertion. Inform the patient that, during the first 3–6 months of Mirena use, the number of bleeding and spotting days may be higher and bleeding patterns may be irregular. If her symptoms continue or are severe, she should report them to her healthcare provider. [See Warnings and Precautions (5.8).]
- Clinical Considerations for Use and Removal: Advise the patient to contact her healthcare provider if she experiences any of the following:
- A stroke or heart attack
- Very severe or migraine headaches
- Unexplained fever
- Yellowing of the skin or whites of the eyes, as these may be signs of serious liver problems
- Pregnancy or suspected pregnancy
- Pelvic pain, abdominal pain, or pain during sex
- HIV positive seroconversion in herself or her partner
- Possible exposure to STIs
- Unusual vaginal discharge or genital sores
- Severe vaginal bleeding or bleeding that lasts a long time, or if she misses a menstrual period
- Inability to feel Mirena's threads

Patient Package Insert

Patient Information
MIRENA® (mur-ā-nah)
(levonorgestrel-releasing intrauterine system)

Read this Patient Information carefully before you decide if MIRENA is right for you. This information does not take the place of talking with your gynecologist or other healthcare provider who specializes in women's health. If you have any questions about MIRENA, ask your healthcare provider. You should also learn about other birth control methods to choose the one that is best for you.

MIRENA does not protect against HIV infection (AIDS) and other sexually transmitted infections (STIs).

What is MIRENA?

- MIRENA is a hormone-releasing system placed in your uterus by your healthcare provider to prevent pregnancy for up to 8 years.
- MIRENA can also be used to decrease menstrual blood loss for up to 5 years in women who have heavy menstrual flow and who also want to use a birth control method that is placed in the uterus to prevent pregnancy.
- MIRENA can be removed by your healthcare provider at any time.
- MIRENA can be used whether or not you have given birth to a child.

MIRENA is a small flexible plastic T-shaped system that slowly releases a progestin hormone called levonorgestrel (LNG) that is often used in birth control pills. Because MIRENA releases LNG into your uterus, only small amounts of the hormone enter your blood. MIRENA does not contain estrogen.

Two thin threads are attached to the stem (lower end) of MIRENA. The threads are the only part of MIRENA you can feel when MIRENA is in your uterus; however, unlike a tampon string, the threads do not extend outside your body.

MIRENA is small

and flexible

What if I need birth control for more than 8 years?

MIRENA must be removed after 8 years. Your healthcare provider can place a new MIRENA during the same office visit if you choose to continue using MIRENA.

What if I need treatment for heavy menstrual flow for more than 5 years?

For continued treatment of heavy menstrual flow after 5 years, your healthcare provider can remove MIRENA and place a new MIRENA during the same office visit.

What if I want to stop using MIRENA?

MIRENA is intended for use up to 8 years, but you can stop using MIRENA at any time by asking your healthcare provider to remove it. You could become pregnant as soon as MIRENA is removed, so you should use another method of birth control if you do not want to become pregnant. Talk to your healthcare provider about the best birth control methods for you, because your new method may need to be started 7 days before MIRENA is removed to prevent pregnancy.

What if I change my mind about birth control and want to become pregnant in less than 8 years?

Your healthcare provider can remove MIRENA at any time. You may become pregnant as soon as MIRENA is removed. About 8 out of 10 women who want to become pregnant will become pregnant sometime in the first year after MIRENA is removed.

How does MIRENA work?

MIRENA may work in several ways including thickening cervical mucus, inhibiting sperm movement, reducing sperm survival, and thinning the lining of your uterus. It is not known exactly how these actions work together to prevent pregnancy.

MIRENA can cause your menstrual bleeding to be less by thinning the lining of the uterus.

How well does MIRENA work for contraception?

The following chart shows the chance of getting pregnant for women who use different methods of birth control. Each box on the chart contains a list of birth control methods that are similar in effectiveness. The most effective methods are at the top of the chart. The box on the bottom of the chart shows the chance of getting pregnant for women who do not use birth control and are trying to get pregnant.

MIRENA, an intrauterine device (IUD), also known as an intrauterine system (IUS), is in the box at the top of the chart.

How well does MIRENA work for heavy menstrual bleeding?

In the clinical trial performed in women with heavy menstrual bleeding and treated with MIRENA, almost 9 out of 10 were treated successfully and their blood loss was reduced by more than half.

Who might use MIRENA?

You might choose MIRENA if you:

- want long-term birth control that provides a low chance of getting pregnant (less than 1 in 100)
- want birth control that works continuously for up to 8 years
- want birth control that is reversible
- want a birth control method that you do not need to take daily
- want treatment for heavy periods up to 5 years and are willing to use a birth control method that is placed in the uterus
- want birth control that does not contain estrogen

Do not use MIRENA if you:

- are or might be pregnant; MIRENA cannot be used as an emergency contraceptive
- have a serious pelvic infection called pelvic inflammatory disease (PID) or have had PID in the past unless you have had a normal pregnancy after the infection went away
- have an untreated genital infection now
- have had a serious pelvic infection in the past 3 months after a pregnancy
- can get infections easily. For example, if you:
  - have multiple sexual partners or your partner has multiple sexual partners
  - have problems with your immune system
  - use or abuse intravenous drugs
- have or suspect you might have cancer of the uterus or cervix
- have bleeding from the vagina that has not been explained
- have liver disease or a liver tumor
- have breast cancer or any other cancer that is sensitive to progestin (a female hormone), now or in the past
- have an intrauterine device in your uterus already
- have a condition of the uterus that changes the shape of the uterine cavity, such as large fibroid tumors
- are allergic to levonorgestrel, silicone, polyethylene, silica, barium sulfate or iron oxide

Before having MIRENA placed, tell your healthcare provider about all of your medical conditions including if you:

- have any of the conditions listed above
- have had a heart attack
- have had a stroke
- were born with heart disease or have problems with your heart valves
- have problems with blood clotting or take medicine to reduce clotting
- have high blood pressure
- recently had a baby or are breastfeeding
- have severe headaches or migraine headaches
- have AIDS, HIV, or any other sexually transmitted infection

Tell your healthcare provider about all of the medicines you take, including prescription and over-the-counter medicines, vitamins, and herbal supplements.

How is MIRENA placed?

MIRENA is placed by your healthcare provider during an in-office visit or immediately after giving birth.

First, your healthcare provider will examine your pelvis to find the exact position of your uterus. Your healthcare provider will then clean your vagina and cervix with an antiseptic solution and slide a slim plastic tube containing MIRENA through the cervix into your uterus. Your healthcare provider will then remove the plastic tube and leave MIRENA in your uterus. Your healthcare provider will cut the threads to the right length.

You may experience pain, bleeding or dizziness during and after placement. If your symptoms do not pass within 30 minutes after placement, MIRENA may not have been placed correctly. Your healthcare provider will examine you to see if MIRENA needs to be removed or replaced.

Should I check that MIRENA is in place?

Yes, you should check that MIRENA is in proper position by feeling the removal threads. It is a good habit to do this 1 time a month. Your healthcare provider should teach you how to check that MIRENA is in place. First, wash your hands with soap and water. You can check by reaching up to the top of your vagina with clean fingers to feel the removal threads. Do not pull on the threads.

If you feel more than just the threads or if you cannot feel the threads, MIRENA may not be in the right position and may not prevent pregnancy. Avoid intercourse or use non-hormonal back-up birth control (such as condoms or spermicide) and ask your healthcare provider to check that MIRENA is still in the right place.

How soon after placement of MIRENA should I return to my healthcare provider?

Call your healthcare provider if you have any questions or concerns (see "When should I call my healthcare provider?"). Otherwise, you should return to your healthcare provider for a follow-up visit 4 to 6 weeks after MIRENA is placed to make sure that MIRENA is in the right position.

Can I use tampons or menstrual cups with MIRENA?

Yes, tampons or menstrual cups may be used with MIRENA. Change tampons or menstrual cups with care to avoid pulling the threads of Mirena. If you think you may have pulled Mirena out of place, avoid intercourse or use a non-hormonal back-up birth control (such as condoms or spermicide), and contact your healthcare provider.

What if I become pregnant while using MIRENA?

Call your healthcare provider right away if you think you may be pregnant. If possible, also do a urine pregnancy test. If you get pregnant while using MIRENA, you may have an ectopic pregnancy. This means that the pregnancy is not in the uterus. Unusual vaginal bleeding or abdominal pain especially with missed periods may be a sign of ectopic pregnancy.

Ectopic pregnancy is a medical emergency that often requires surgery. Ectopic pregnancy can cause internal bleeding, infertility, and even death.

There are also risks if you get pregnant while using MIRENA and the pregnancy is in the uterus. Severe infection, miscarriage, premature delivery, and even death can occur with pregnancies that continue with an intrauterine device (IUD). Because of this, your healthcare provider may try to remove MIRENA, even though removing it may cause a miscarriage. If MIRENA cannot be removed, talk with your healthcare provider about the benefits and risks of continuing the pregnancy and possible effects of the hormone on your unborn baby.

If you continue your pregnancy, see your healthcare provider regularly. Call your healthcare provider right away if you get flu-like symptoms, fever, chills, cramping, pain, bleeding, vaginal discharge, or fluid leaking from your vagina. These may be signs of infection.

How will MIRENA change my periods?

For the first 3 to 6 months, your period may become irregular and the number of bleeding days may increase. You may also have frequent spotting or light bleeding, and some women have heavy bleeding during this time. You may also have cramping during the first few weeks. After you have used MIRENA for a while, the number of bleeding and spotting days is likely to lessen. For some women, periods will stop altogether. When Mirena is removed, your menstrual periods should return.

In some women with heavy bleeding, the total blood loss per cycle progressively decreases with continued use. The number of spotting and bleeding days may initially increase but then typically decreases in the months that follow.

Is it safe to breastfeed while using MIRENA?

You may use MIRENA when you are breastfeeding. MIRENA is not likely to affect the quality or amount of your breast milk or the health of your nursing baby. However, isolated cases of decreased milk production have been reported. The risk of MIRENA going into the wall of the uterus (becoming embedded) or going through the wall of the uterus is increased if MIRENA is inserted while you are breastfeeding.

Will MIRENA interfere with sexual intercourse?

You and your partner should not feel MIRENA during intercourse. MIRENA is placed in the uterus, not in the vagina. Sometimes your partner may feel the threads. If this occurs, or if you or your partner experience pain during sex, talk with your healthcare provider.

What are the possible side effects of MIRENA?

MIRENA can cause serious side effects including:

- Ectopic pregnancy and intrauterine pregnancy risks. There are risks if you become pregnant while using Mirena (see "What if I become pregnant while using Mirena?").
- Life-threatening infection. Life-threatening infection can occur within the first few days after MIRENA is placed. Call your healthcare provider immediately if you develop severe pain or fever shortly after MIRENA is placed.
- Pelvic inflammatory disease (PID). Some IUD users get a serious pelvic infection called pelvic inflammatory disease. PID is usually sexually transmitted. You have a higher chance of getting PID if you or your partner has sex with other partners. PID can cause serious problems such as infertility, ectopic pregnancy or pelvic pain that does not go away. PID is usually treated with antibiotics. More serious cases of PID may require surgery including removal of the uterus (hysterectomy). In rare cases, infections that start as PID can even cause death.
Tell your healthcare provider right away if you have any of these signs of PID: long-lasting or heavy bleeding, unusual vaginal discharge, low abdominal (stomach area) pain, painful sex, chills, fever, genital lesions or sores.
- Perforation. MIRENA may go into the wall of the uterus (become embedded) or go through the wall of the uterus. This is called perforation. If this occurs, MIRENA may no longer prevent pregnancy. If perforation occurs, MIRENA may move outside the uterus and can cause internal scarring, infection, or damage to other organs, and you may need surgery to have MIRENA removed. Excessive pain or vaginal bleeding during placement of MIRENA, pain or bleeding that gets worse after placement, or not being able to feel the threads may happen with perforation. The risk of perforation is increased if MIRENA is inserted while you are breastfeeding, or if you have recently given birth.
- Expulsion. MIRENA may come out by itself. This is called expulsion. Excessive pain or vaginal bleeding during placement of MIRENA, pain or bleeding that gets worse after placement, or not being able to feel the threads may happen with expulsion. You may become pregnant if MIRENA comes out. If you think that MIRENA has come out, avoid intercourse or use a non-hormonal back-up birth control (such as condoms or spermicide) and call your healthcare provider. The risk of expulsion is increased with insertion right after delivery or second-trimester abortion.

Common side effects of Mirena include:

- Pain, bleeding or dizziness during and after placement. If these symptoms do not stop 30 minutes after placement, MIRENA may not have been placed correctly. Your healthcare provider will examine you to see if MIRENA needs to be removed or replaced.
- Changes in bleeding. You may have bleeding and spotting between menstrual periods, especially during the first 3 to 6 months. Sometimes the bleeding is heavier than usual at first. However, the bleeding usually becomes lighter than usual and may be irregular. Call your healthcare provider if the bleeding remains heavier than usual or increases after it has been light for a while.
- Missed menstrual periods. About 2 out of 10 women stop having periods after 1 year of MIRENA use. If you have any concerns that you may be pregnant while using MIRENA, do a urine pregnancy test and call your healthcare provider. If you do not have a period for 6 weeks during MIRENA use, call your healthcare provider. When MIRENA is removed, your menstrual periods should return.
- Cysts on the ovary. Some women using MIRENA develop a painful cyst on the ovary. These cysts usually disappear on their own in 2 to 3 months. However, cysts can cause pain and sometimes cysts will need surgery.

Other common side effects include:

- abdominal or pelvic pain
- inflammation or infection of the outer part of your vagina (vulvovaginitis)
- headache or migraine
- vaginal discharge

These are not all of the possible side effects with MIRENA. For more information, ask your healthcare provider.

Call your doctor for medical advice about side effects. You may report side effects to FDA at 1-800-FDA-1088. You may also report side effects to Bayer Healthcare Pharmaceuticals at 1-888-842-2937.

After MIRENA has been placed, when should I call my healthcare provider?

If Mirena is accidentally removed and you had vaginal intercourse within the preceding week, you may be at risk of pregnancy, and you should talk to a healthcare provider.

Call your healthcare provider if you have any concerns about MIRENA. Be sure to call if you:

- think you are pregnant
- have pelvic pain, abdominal pain or pain during sex
- have unusual vaginal discharge or genital sores
- have unexplained fever, flu-like symptoms or chills
- might be exposed to sexually transmitted infections (STIs)
- are concerned that Mirena may have been expelled (came out)
- cannot feel MIRENA's threads
- develop very severe or migraine headaches
- have yellowing of the skin or whites of the eyes. These may be signs of liver problems.
- have had a stroke or heart attack
- become HIV positive or your partner becomes HIV positive
- have severe vaginal bleeding or bleeding that lasts a long time or concerns you

General advice about the safe and effective use of MIRENA.

Medicines are sometimes prescribed for purposes other than those listed in patient information leaflets. If you would like more information, talk with your healthcare provider. You can ask your healthcare provider for information about MIRENA that is written for health professionals.

What are the ingredients in MIRENA?

Active ingredient: levonorgestrel

Inactive ingredients: silicone, polyethylene, silica, barium sulfate, iron oxide

Manufactured for:

Bayer HealthCare Pharmaceuticals Inc.
Whippany, NJ 07981

© 2000, Bayer HealthCare Pharmaceuticals Inc.
All rights reserved.

For more information, go to www.MIRENA-us.com or call 1-888-842-2937

This Patient Information has been approved by the U.S. Food and Drug Administration. 8/2022

PRINCIPAL DISPLAY PANEL - 52 mg Intrauterine System Carton

NDC 50419-423-01
1 Sterile Unit
Rx only

IMPORTANT: To be inserted in the uterus
by a trained healthcare provider. Mirena
cannot be reloaded. See physician insert
for detailed instructions for use.

Contains single-handed inserter
with no visible removal threads.

Mirena®
(levonorgestrel-releasing intrauterine system)
52 mg